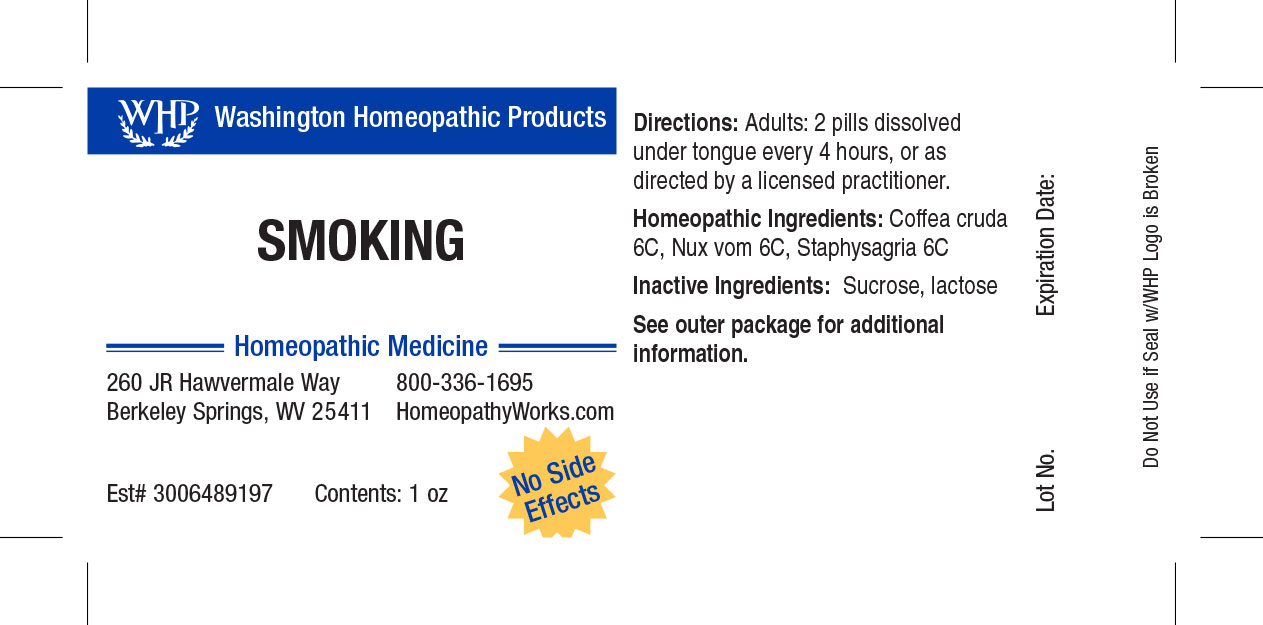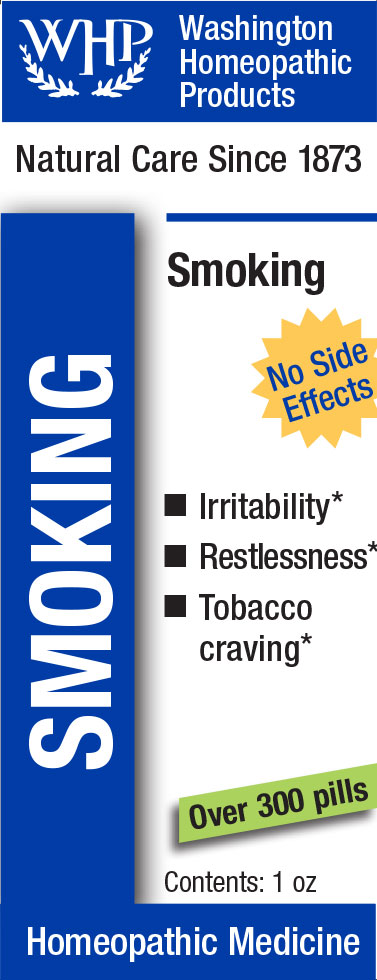 DRUG LABEL: WHP Smoking
NDC: 71919-805 | Form: PELLET
Manufacturer: Washington Homeopathic Products
Category: homeopathic | Type: HUMAN OTC DRUG LABEL
Date: 20250128

ACTIVE INGREDIENTS: DELPHINIUM STAPHISAGRIA SEED 6 [hp_C]/1 1; STRYCHNOS NUX-VOMICA SEED 6 [hp_C]/1 1; ARABICA COFFEE BEAN 6 [hp_C]/1 1
INACTIVE INGREDIENTS: LACTOSE; SUCROSE

WHP Smoking

ACTIVE INGREDIENTS

COFFEA CRUDA 6C

NUX VOM 6C

STAPHYSAG 6C

USES

Temporarily relieves headaches.

KEEP OUT OF REACH OF CHILDREN

As with all medications, keep out of reach of children.

INDICATIONS

COFFEA CRUDA Sleeplessness

NUX VOM Vomiting

STAPHYSAG Anger

STOP USE AND ASK DOCTOR

If symptoms persist or recur, discontinue use. If pregnant or nursing, consult a licensed practitioner before using this product.

DIRECTIONS

Directions: Adults and children 12 years and older: 2 pills dissolved under tongue every 4 hours, or as directed by a licensed practitioner. Children 4 years to under 12 years: 1 pill dissolved under tongue every 4 hours, or as directed by a licensed practitioner. Children under 4 years: Consult a licensed practitioner.

INACTIVE INGREDIENTS

Sucrose/Lactose